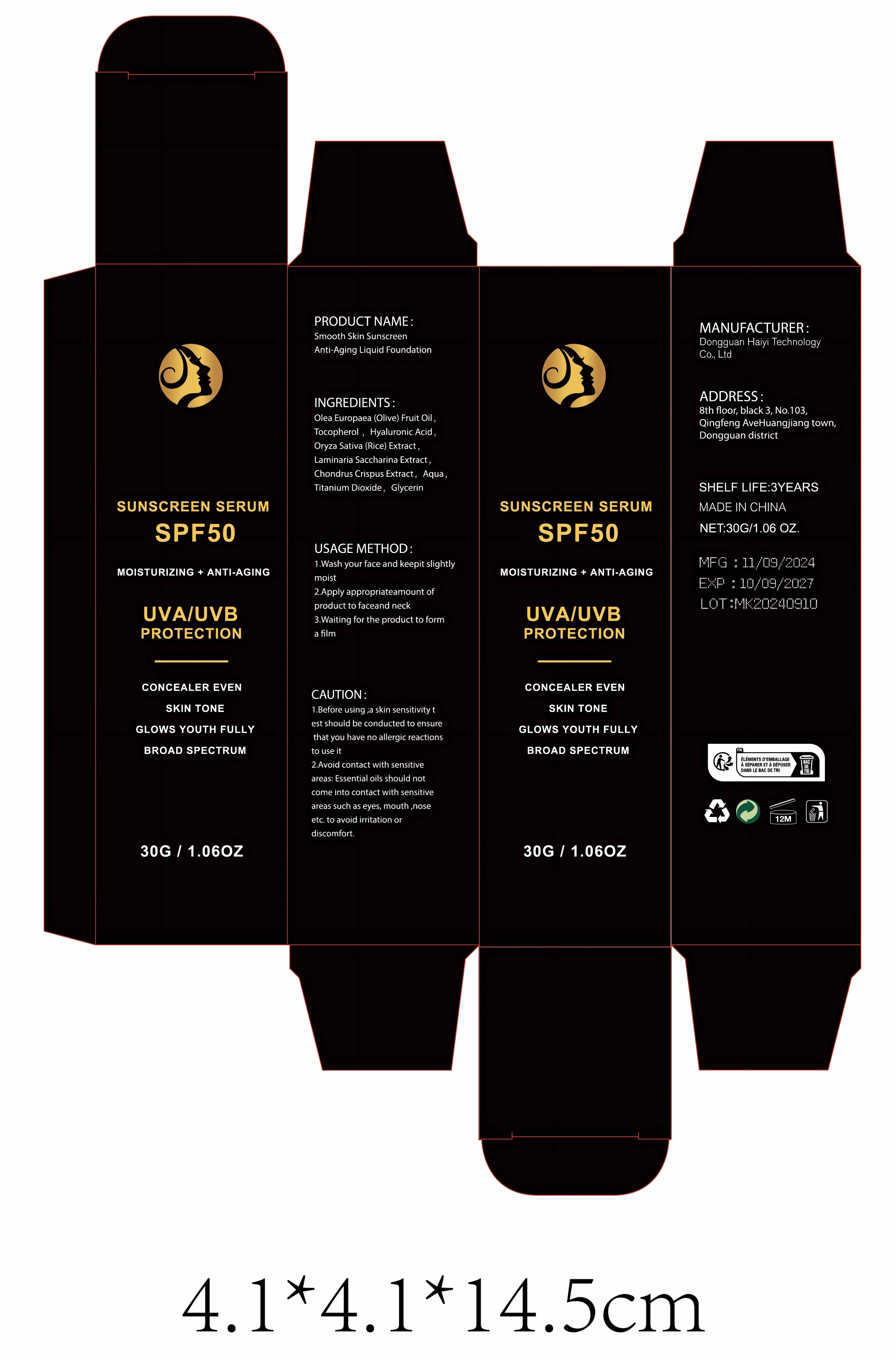 DRUG LABEL: Smooth Skin Sunscreen Anti-Aging Liquid Foundation
NDC: 84732-050 | Form: LIQUID
Manufacturer: Dongguan Haiyi Technology Co.,Ltd.
Category: otc | Type: HUMAN OTC DRUG LABEL
Date: 20241016

ACTIVE INGREDIENTS: HYALURONIC ACID 1 mg/100 g; OLIVE OIL 1 mg/100 g; .ALPHA.-TOCOPHEROL 1 mg/100 g
INACTIVE INGREDIENTS: CHONDRUS CRISPUS CARRAGEENAN; WATER; TITANIUM DIOXIDE; RICE MIDDLINGS; GLYCERIN; SACCHARINA LATISSIMA

Active ingredient

Olea Europaea (Olive) Fruit Oil ,Tocopherol , Hyaluronic Acid

Inactive ingredient

Oryza Sativa (Rice) Extract ,Laminaria Saccharina Extract,Chondrus Crispus Extract, Aqua,Titanium Dioxide, Glycerin

Purpose section

Conceal: Covers blemishes, spots, and uneven skin tone.

Evens skin tone: Helps even out skin tone, making skin look smoother and more consistent.

Provides hydration: Some foundations contain moisturizing ingredients to help keep skin hydrated.
Protects skin: Some foundations contain sunscreen ingredients to protect skin from UV rays.
Improves makeup durability: Foundation helps makeup last longer and is less likely to come off.

Warning

1.Before using ;a skin sensitivity test should be conducted to ensurethat you have no alergic reactionsto use it
2.Avoid contact with sensitiveareas: Essential oils should notcome into contact with sensitiveareas such as eyes, mouth ,noseetc. to avoid irritation or discomfort.

stop use

This product may cause allergic reactions in asmall number of people.
lf you experience any discomfort,please stop using it immediately.

not use

Not suitable for use by children, pregnantor breast feeding people.

OUT OF CHILDREN

KEEP THE PRODUCT OUT OF REACH OF CHILDREN to

HOW TO USE

1.Wash your face and keepit slightly moist
2.Apply appropriateamount ofproduct to faceand neck

3.Waiting for the product to forma flm

Dosage

1.Facial coverage: Usually squeeze out an appropriate amount of liquid foundation (about the size of a pea), depending on specific needs. If you need stronger concealer, you can build up layers without applying too much at once.

2.Even distribution: Use a makeup brush, sponge, or fingers to apply liquid foundation evenly on the face, especially in areas that need concealer, such as the forehead, nose, chin, and cheeks.

3.Appropriate adjustment: The specific amount used depends on personal skin type, coverage needs, and the texture of liquid foundation.